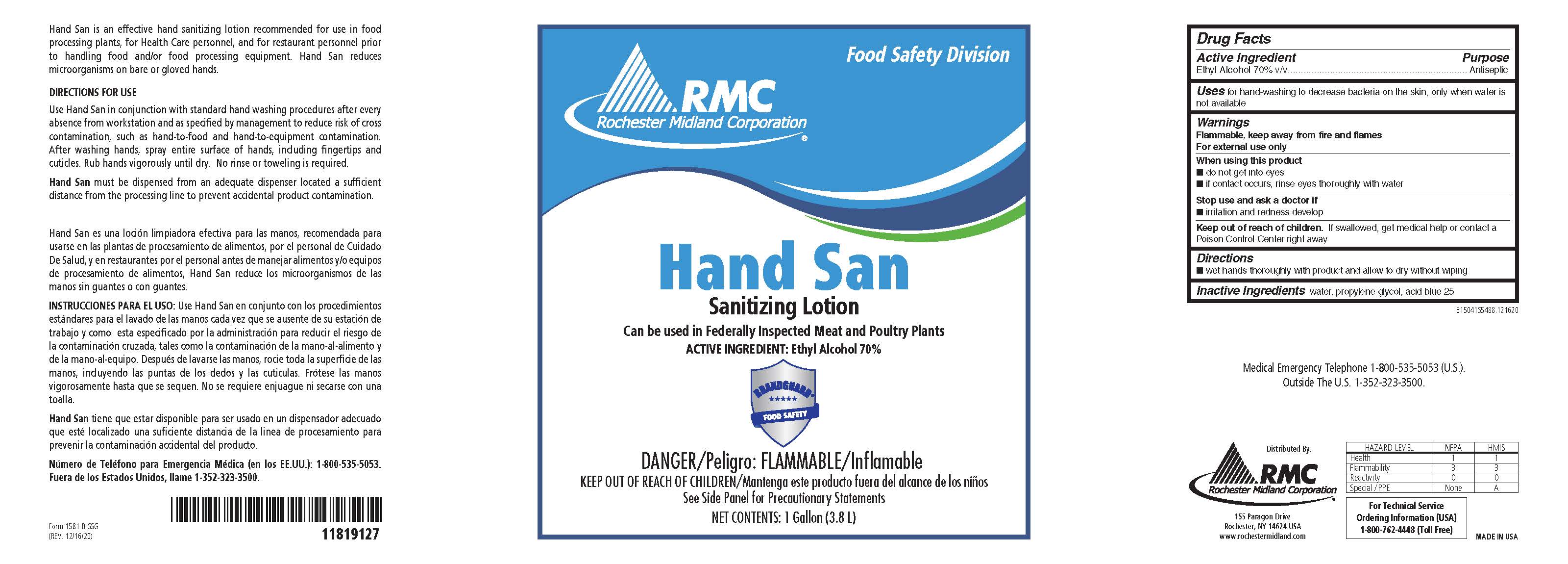 DRUG LABEL: Hand San
NDC: 59503-2605 | Form: LIQUID
Manufacturer: Rochester Midland Corporation
Category: otc | Type: HUMAN OTC DRUG LABEL
Date: 20251118

ACTIVE INGREDIENTS: ALCOHOL 0.7 mL/1 mL
INACTIVE INGREDIENTS: WATER; PROPYLENE GLYCOL; ACID BLUE 25

Hand San 6150 Drug Facts and Label

Drug Facts Box OTC-Active Ingredient Section

Ethyl Alcohol 70% v/v

Drug Facts Box OTC-Purpose Section

Antiseptic

Drug Facts Box OTC-Indications and Usage Section

for hand-washing to decrease bacteria on the skin, only when water is not available

Drug Facts Box OTC-Warnings Section

Flammable, keep away from fire and flames

For external use only

Drug Facts Box OTC-When Using Section

do not get into eyes

if contact occurs, rinse eyes thoroughly with water

Drug Facts Box OTC-Stop Use Section

irritation and redness develop

Drug Facts Box OTC-Keep Out of Reach of Children Section

If swallowed, get medical help or contact a Poison Control Center right away

Drug Facts Box OTC-Dosage & Administration Section

Wet hands thoroughly with product and allow to dry without wiping

Drug Facts Box OTC-Inactive Ingredient Section

water, propylene glycol, acid blue 25

Hand San 6150

Hand Aid 6150 Rochester Midland